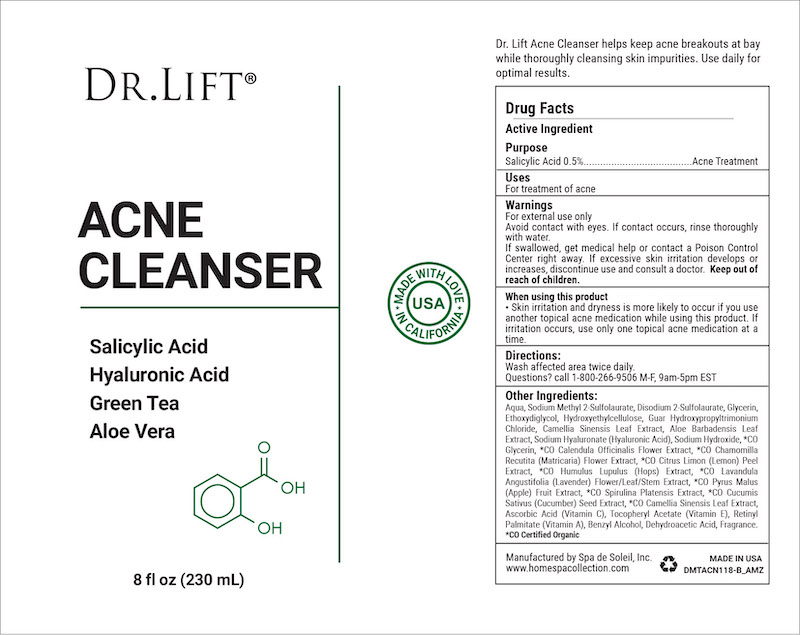 DRUG LABEL: Dr. Lift Acne Cleanser
NDC: 68062-2263 | Form: LIQUID
Manufacturer: Spa de Soleil
Category: otc | Type: HUMAN OTC DRUG LABEL
Date: 20260121

ACTIVE INGREDIENTS: SALICYLIC ACID 1.15 mg/230 mL
INACTIVE INGREDIENTS: SODIUM METHYL 2-SULFOLAURATE; DISODIUM 2-SULFOLAURATE; WATER; GLYCERIN

Dr Lift Acne Cleanser

Active ingredient Purpose

Salicylic Acid (0.5%)..........Acne Treatment

Purpose

Acne Treatment

INDICATIONS AND USAGE

For treatment of acne

Warnings

For external use only

Avoid contact with eyes. If contact occurs, rinse thoroughly with water.

If swallowed, get medical help or contact a Poison Control Center right away. If excessive skin irritation develops or increases, discontinue use and consult a doctor. Keep out of reach of children.

Keep out of reach of children. In case of accidental ingestion, get medical help or contact a Poison Control Center right away.

When using this product

• Skin irritation and dryness is more likely to occur if you use another topical acne medication while using this product. If irritation occurs, use only one topical acne medication at a time.

Directions:

Wash affected area twice daily.

INACTIVE INGREDIENT

Other Ingredients:

Aqua, Sodium Methyl 2-Sulfolaurate, Disodium 2-Sulfolaurate, Glycerin, Ethoxydiglycol, Hydroxyethylcellulose, Guar Hydroxypropyltrimonium Chloride, Camellia Sinensis Leaf Extract, Aloe Barbadensis Leaf Extract, Sodium Hyaluronate (Hyaluronic Acid), Sodium Hydroxide, *CO Glycerin, *CO Calendula Officinalis Flower Extract, *CO Chamomilla Recutita (Matricaria) Flower Extract, *CO Citrus Limon (Lemon) Peel Extract, *CO Humulus Lupulus (Hops) Extract, *CO Lavandula Angustifolia (Lavender) Flower/Leaf/Stem Extract, *CO Pyrus Malus (Apple) Fruit Extract, *CO Spirulina Platensis Extract, *CO Cucumis Sativus (Cucumber) Seed Extract, *CO Camellia Sinensis Leaf Extract, Ascorbic Acid (Vitamin C), Tocopheryl Acetate (Vitamin E), Retinyl Palmitate (Vitamin A), Benzyl Alcohol, Dehydroacetic Acid, Fragrance. *CO Certified Organic